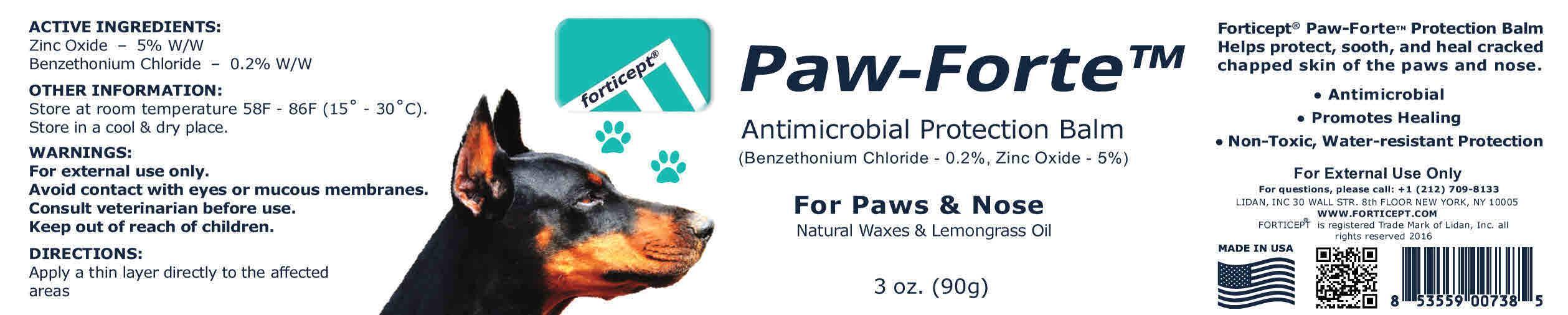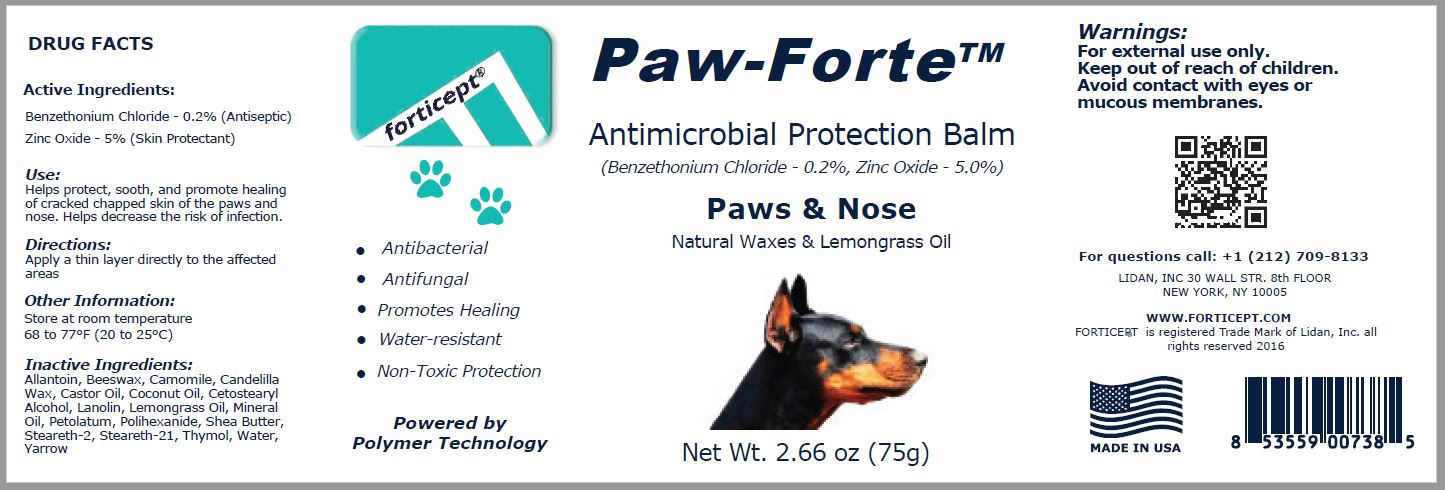 DRUG LABEL: Forticept Paw-Forte
NDC: 72127-0708 | Form: OINTMENT
Manufacturer: Lidan, Inc.
Category: animal | Type: OTC ANIMAL DRUG LABEL
Date: 20230105

ACTIVE INGREDIENTS: BENZETHONIUM CHLORIDE 0.002 kg/1 kg; ZINC OXIDE 0.05 kg/1 kg
INACTIVE INGREDIENTS: ALLANTOIN; YELLOW WAX; CHAMOMILE; CANDELILLA WAX; CASTOR OIL; COCONUT OIL; CETOSTEARYL ALCOHOL; Lanolin; EAST INDIAN LEMONGRASS OIL; MINERAL OIL; PETROLATUM; POLIHEXANIDE; SHEA BUTTER; STEARETH-2; STEARETH-21; THYMOL; WATER; ACHILLEA MILLEFOLIUM WHOLE

FORTICEPT PAW-FORTE ANTIMICROBIAL PROTECTION BALM

Active Ingredients:

Benzethonium Chloride - 0.2% (Antimicrobial)
Zinc Oxide - 5% (Skin Protectant)

Uses:

Helps protect, sooth, and heal cracked chapped skin of the paws and nose.

Warnings:

For external use only
Avoid contact with eyes or mucous membranes
Consult veterinarian before use
Keep out of reach of children

Directions:

Apply a thin layer directly to the affected areas

Other Information:

Store at room temperature 58F - 86F (15˚ - 30˚C)
Store in a cool & dry place